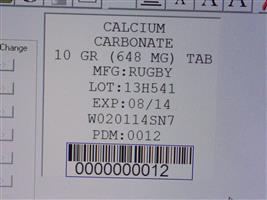 DRUG LABEL: Calcium carbonate
                                    
NDC: 68151-0012 | Form: TABLET
Manufacturer: Carilion Materials Management
Category: otc | Type: HUMAN OTC DRUG LABEL
Date: 20121213

ACTIVE INGREDIENTS: CALCIUM CARBONATE 648 mg/1 1
INACTIVE INGREDIENTS: CROSCARMELLOSE SODIUM; MAGNESIUM STEARATE; MALTODEXTRIN; CELLULOSE, MICROCRYSTALLINE; STEARIC ACID

Calcium Carbonate Tablets

Active Ingredient

(in each tablet)

Calcium carbonate 10 gr (648 mg)

Purpose

Antacid

Use

relieves

- acid indigestion
- heartburn
- sour stomach
- upset stomach associated with these symptoms

Warnings

taking a prescription drug. Antacids may interact with certain prescription drugs. Ask a doctor or pharmacist before use if you are

symptoms last more than 2 weeks. Stop use and ask a doctor if

, ask a health professional before use. If pregnant or breast-feeding

Keep out of reach of children.

Directions

- take one to four tablets daily
- do not take more than 4 tablets in 24 hours
- do not use the maximum dosage for more than 2 weeks

Other Information

- Each tablet contains: calcium 260 mg

- store at room temperature 15°-30°C (59°-86°F)

Inactive Ingredients

croscarmellose sodium, magnesium sterate, maltodextrin, microcrystalline cellulose, stearic acid

Questions or Comments

Call Monday – Friday, 9 am – 5 pm ET 1-800-645-2158,

TAMPER EVIDENT: DO NOT USE IF IMPRINTED SEAL UNDER CAP IS BROKEN OR MISSING

This is a bulk pakage, dispense contents with a child-resistant closure in a tight, light-resistant container as defined in the USP.

Mfd for: Rugby Laboratories,Inc